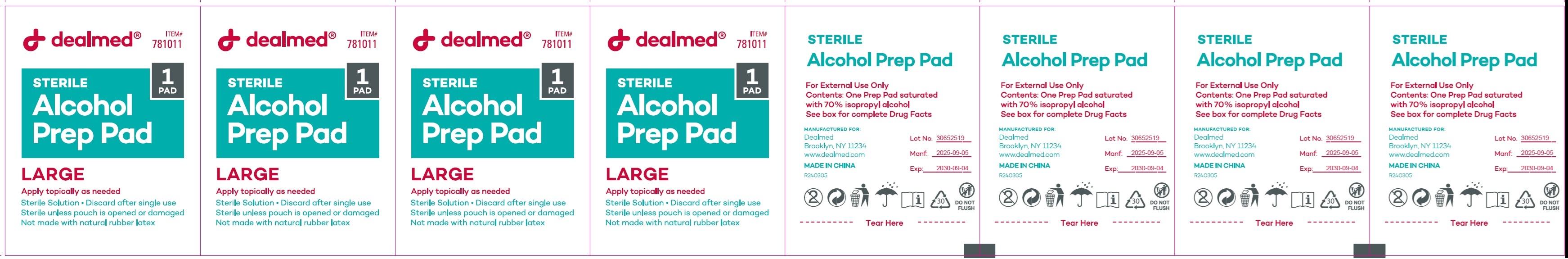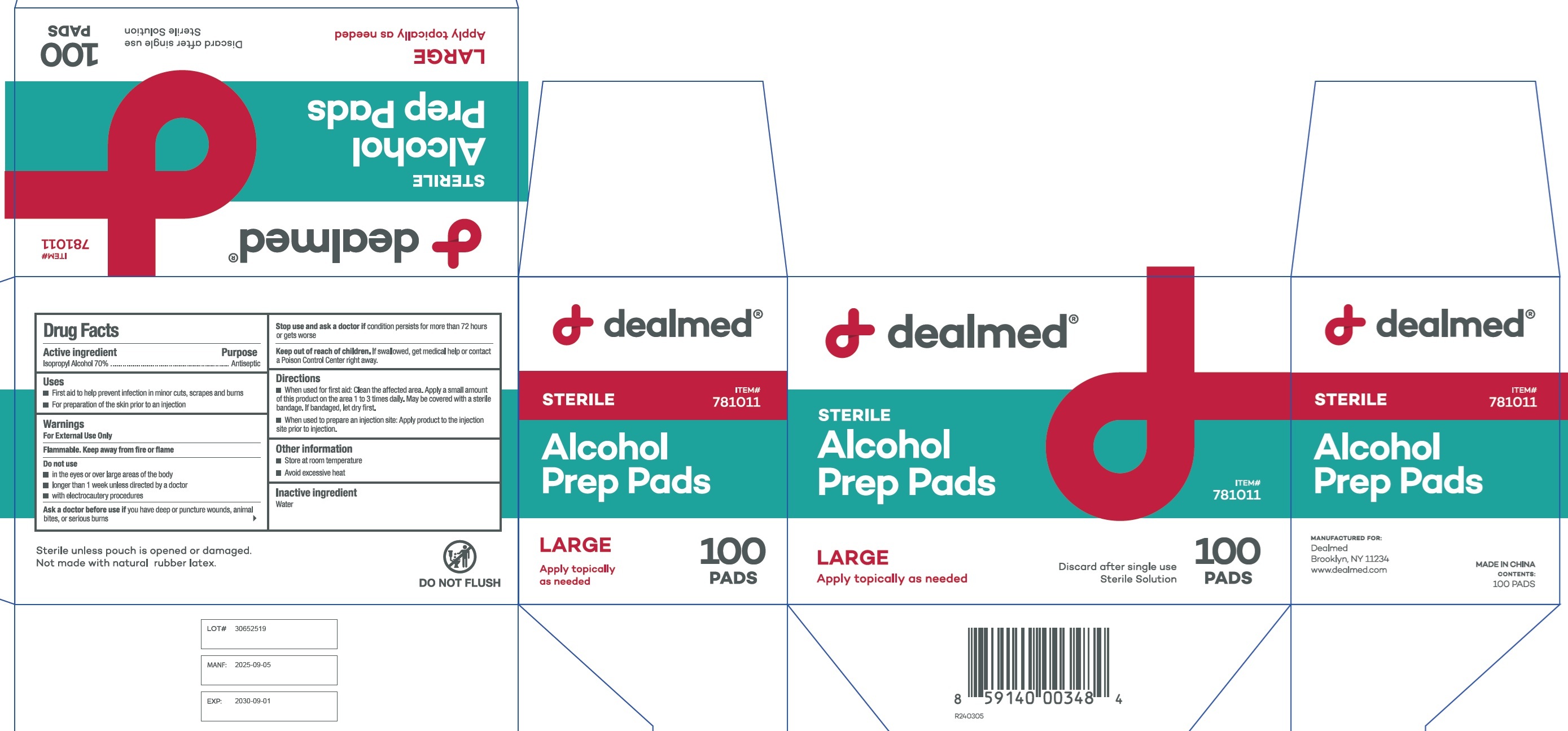 DRUG LABEL: Dealmed Sterile Alcohol Prep Pads Large
NDC: 70082-010 | Form: CLOTH
Manufacturer: Dealmed Medical Supplies, LLC.
Category: otc | Type: HUMAN OTC DRUG LABEL
Date: 20260202

ACTIVE INGREDIENTS: ISOPROPYL ALCOHOL 70 mL/100 mL
INACTIVE INGREDIENTS: WATER

Dealmed Sterile Alcohol Prep Pads Large

Active ingredient

Isopropyl Alcohol 70%

Purpose

Antiseptic

Uses

- First aid to help prevent infection in minor cuts, scrapes and burns
- For preparation of the skin prior to an injection

Warnings

For External Use Only

Flammable. Keep away from fire or flame

Do not use

- in the eyes or over large areas of the body
- longer than 1 week unless directed by a doctor
- with electrocautery procedures

Ask a doctor before use if

you have deep or puncture wounds, animal bites, or serious burns

Stop use and ask a doctor if

condition persists for more than 72 hours or gets worse

Keep out of reach of children.

If swallowed, get medical help or contact a Poison Control Center right away.

Directions

- When used for first aid: Clean the affected area. Apply a small amount of this product on the area 1 to 3 times daily. May be covered with a sterile bandage. If bandaged, let dry first.
- When used to prepare an injection site: Apply product to the injection site prior to injection.

Other information

- Store at room temperature
- Avoid excessive heat

Inactive ingredient

Water